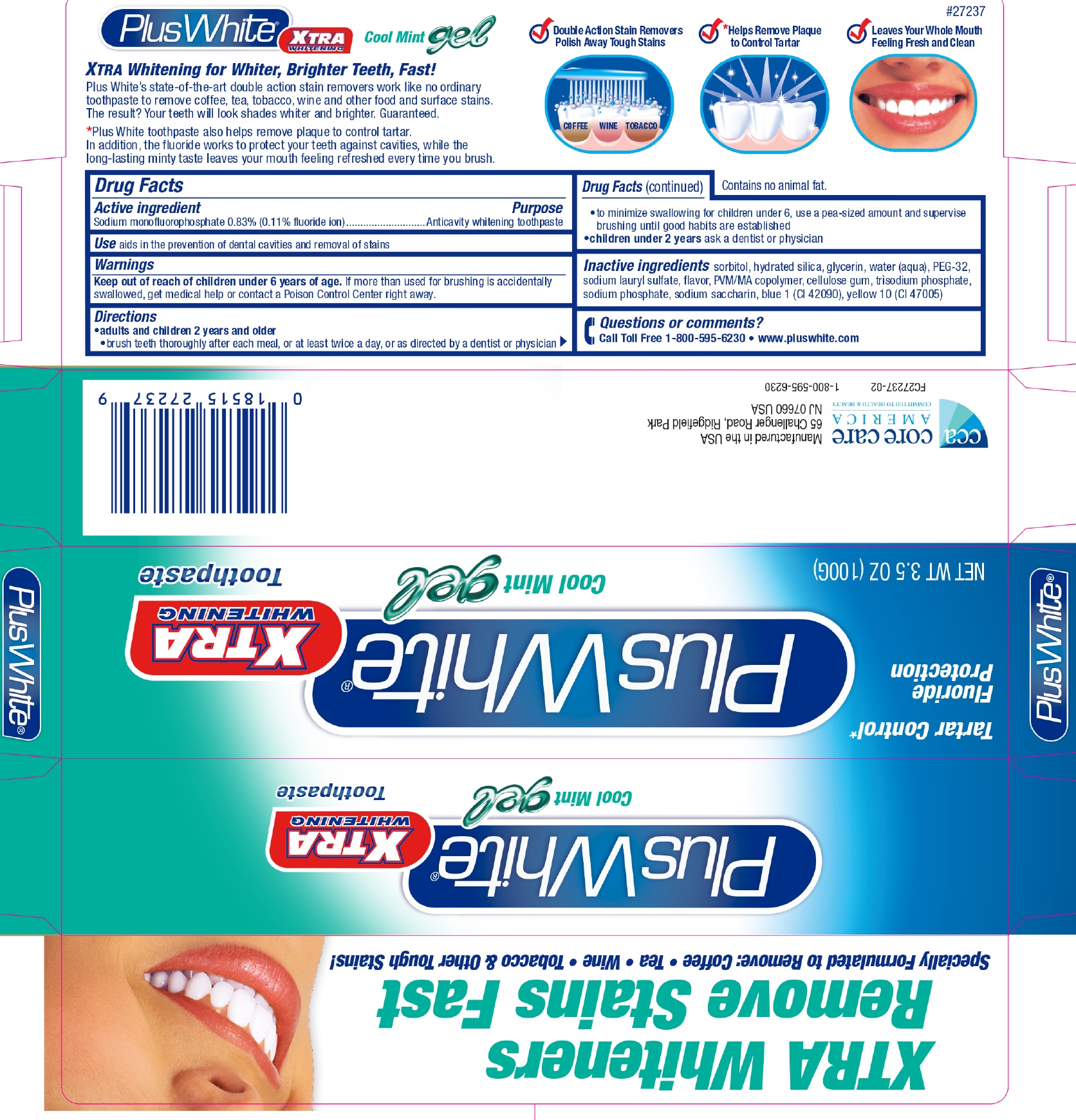 DRUG LABEL: Plus White Xtra
NDC: 61543-7237 | Form: PASTE
Manufacturer: CCA Industries, Inc.
Category: otc | Type: HUMAN OTC DRUG LABEL
Date: 20210813

ACTIVE INGREDIENTS: SODIUM MONOFLUOROPHOSPHATE 1.1 mg/1 g
INACTIVE INGREDIENTS: SORBITOL; HYDRATED SILICA; GLYCERIN; WATER; SODIUM LAURYL SULFATE; CARBOXYMETHYLCELLULOSE SODIUM; SODIUM PHOSPHATE; SACCHARIN SODIUM; FD&C BLUE NO. 1; D&C YELLOW NO. 10

Plus White Xtra Gel

Active ingredient

Sodium Monofluorophosphate 0.83% (0.11% fluoride ion)

Purpose

Anticavity whitening toothpaste

Use

aids in the prevention of dental cavities and removal of stains

Warnings

Keep out of reach of children under 6 years of age.

If more than used for burshing is accidentally swallowed, get medical helo or contact a Poison Control Center right away.

Directions

- adults and children 2 years and older
- brush teeth thoroughly after each meal, or at least twice a day, or as directed by a dentist or physician
- to minimize swallowing for children under 6, use a pea-sized amount and supervise brushing until good habits are established
- children under 2 years ask a dentist or physician

Questions or comments?

call Toll Free 1-800-595-6230 • www.pluswhite.com